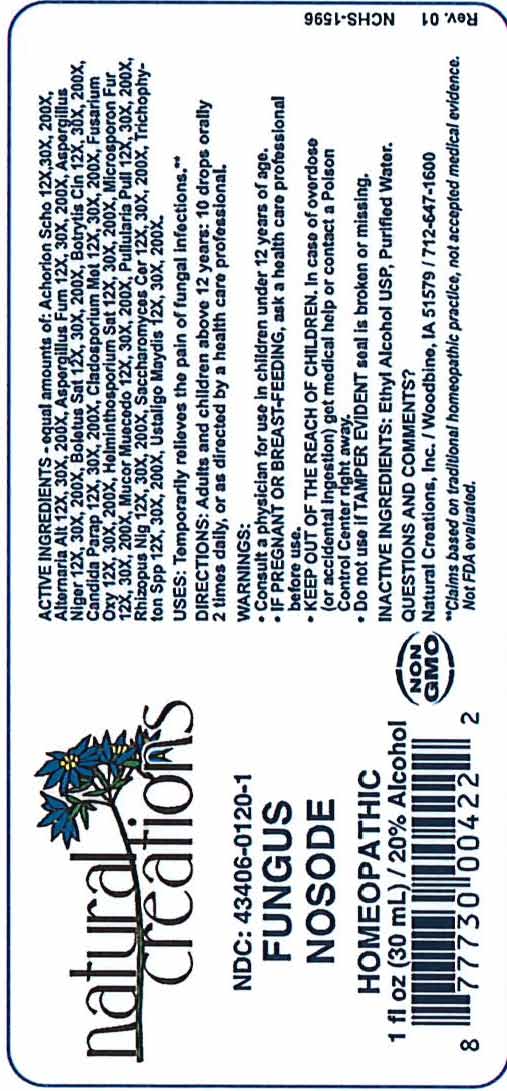 DRUG LABEL: Fungus Nosode
NDC: 43406-0120 | Form: LIQUID
Manufacturer: Natural Creations, Inc
Category: homeopathic | Type: HUMAN OTC DRUG LABEL
Date: 20251210

ACTIVE INGREDIENTS: TRICHOPHYTON SCHOENLEINII 200 [hp_X]/1 mL; ALTERNARIA ALTERNATA 200 [hp_X]/1 mL; ASPERGILLUS FUMIGATUS 200 [hp_X]/1 mL; ASPERGILLUS NIGER VAR. NIGER 200 [hp_X]/1 mL; BOLETUS SATANAS FRUITING BODY 200 [hp_X]/1 mL; BOTRYTIS CINEREA 200 [hp_X]/1 mL; CANDIDA PARAPSILOSIS 200 [hp_X]/1 mL; HORTAEA WERNECKII 200 [hp_X]/1 mL; FUSARIUM OXYSPORUM 200 [hp_X]/1 mL; COCHLIOBOLUS SATIVUS 200 [hp_X]/1 mL; RHIZOPUS STOLONIFER 200 [hp_X]/1 mL; AUREOBASIDIUM PULLULANS VAR. PULLUTANS 200 [hp_X]/1 mL; SACCHAROMYCES CEREVISIAE RNA 200 [hp_X]/1 mL; EPIDERMOPHYTON FLOCCOSUM 200 [hp_X]/1 mL; USTILAGO MAYDIS 200 [hp_X]/1 mL
INACTIVE INGREDIENTS: ALCOHOL; WATER

Fungus Nosode

ACTIVE INGREDIENT

ACTIVE INGREDIENTS - equal amounts of: Achorion Scho 12X,30X,200X, Alternaria Alt 12X,30X,200X, Aspergillus Fum 12X,30X,200X, Aspergillus Niger 12X,30X,200X, Boletus Sat 12X,30X,200X, Botrytis Cin 12X,30X,200X, Candida Parap 12X,30X,200X, Cladosporium Met 12X,30X,200X, Fusarium Oxy 12X,30X,200X, Helminthosporium Sat 12X,30X,200X, Microsporon Fur 12X,30X,200X, Mucor Muecedo 12X,30X,200X, Pullularia Pull 12X,30X,200X, Rhizopus Nig 12X,30X,200X, Saccharomyces Cer 12X,30X,200X, Trichophyton Spp 12X,30X,200X, Ustilago Maydis 12X,30X,200X

INDICATIONS AND USAGE

USES: Temporarily relieves the pain of fungal infections.**

PURPOSE

USES: Temporarily relieves the pain of fungal infections.**

DOSAGE AND ADMINISTRATION

DIRECTIONS: Adults & children above 12 years: 10 drops orally 2 times daily, or as directed by a health care professional.

KEEP OUT OF REACH OF CHILDREN

KEEP OUT OF THE REACH OF CHILDREN. In case of overdose (or accidental ingestion) get medical help or contact a Poison Control Center right away.

WARNINGS:

- Consult a physician for use in children under 12 years of age.
- IF PREGNANT OR BREAST-FEEDING, ask a health care professional before use.
- KEEP OUT OF THE REACH OF CHILDREN. In case of overdose (or accidental ingestion) get medical help or contact a Poison Control Center right away.
- Do not use if TAMPER EVIDENT seal is broken or missing.

INACTIVE INGREDIENTS: Ethyl Alcohol USP, Purified Water

QUESTIONS & COMMENTS?

Natural Creations, Inc. / Woodbine, IA 51579 / 712-647-1600

REFERENCES

**Claims based on traditional homeopathic practice, not accepted medical evidence. Not FDA evaluated.

PACKAGE LABEL

NDC:43406-0120-1

Fungus Nosode

HOMEOPATHIC

1 fl oz (30mL) / 20% Alcohol